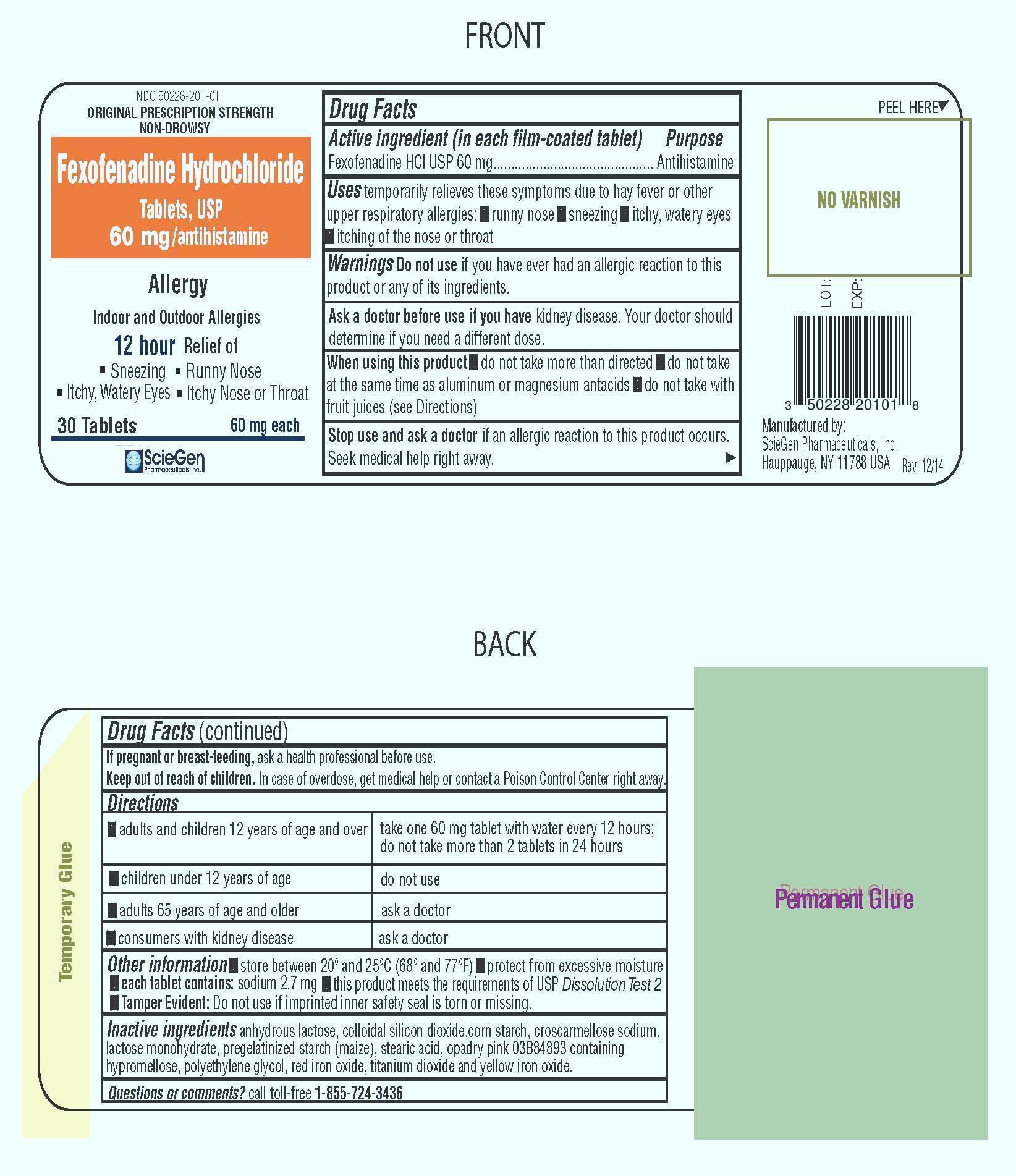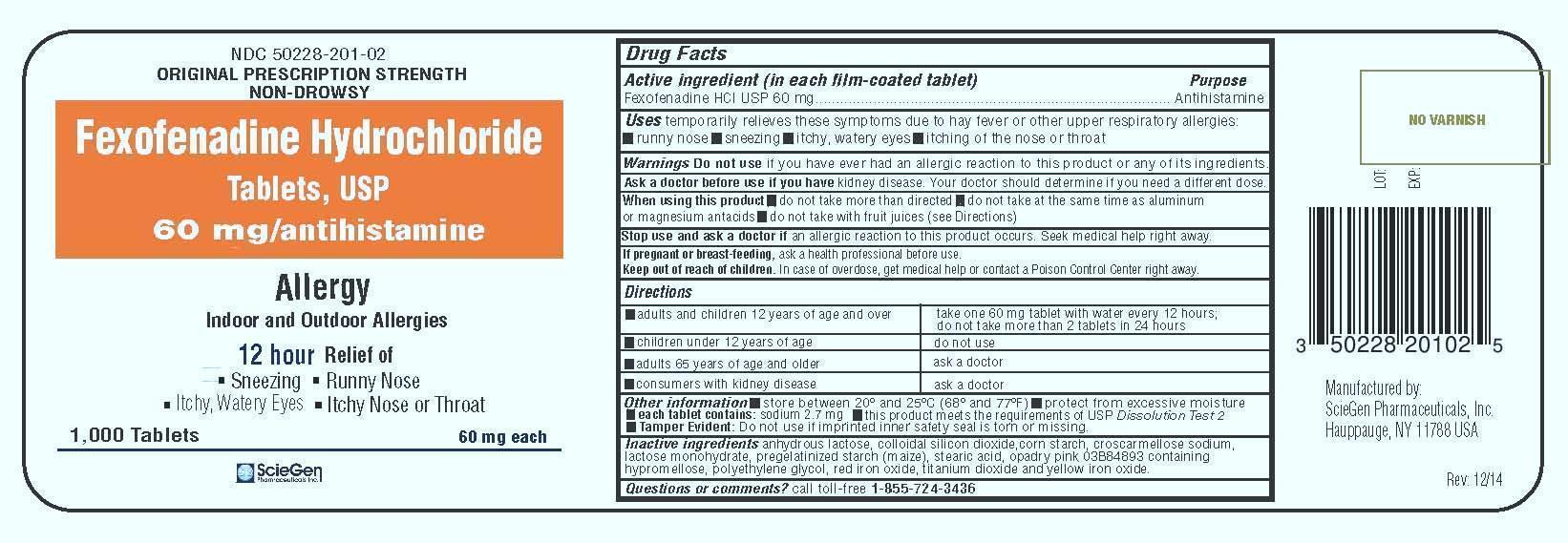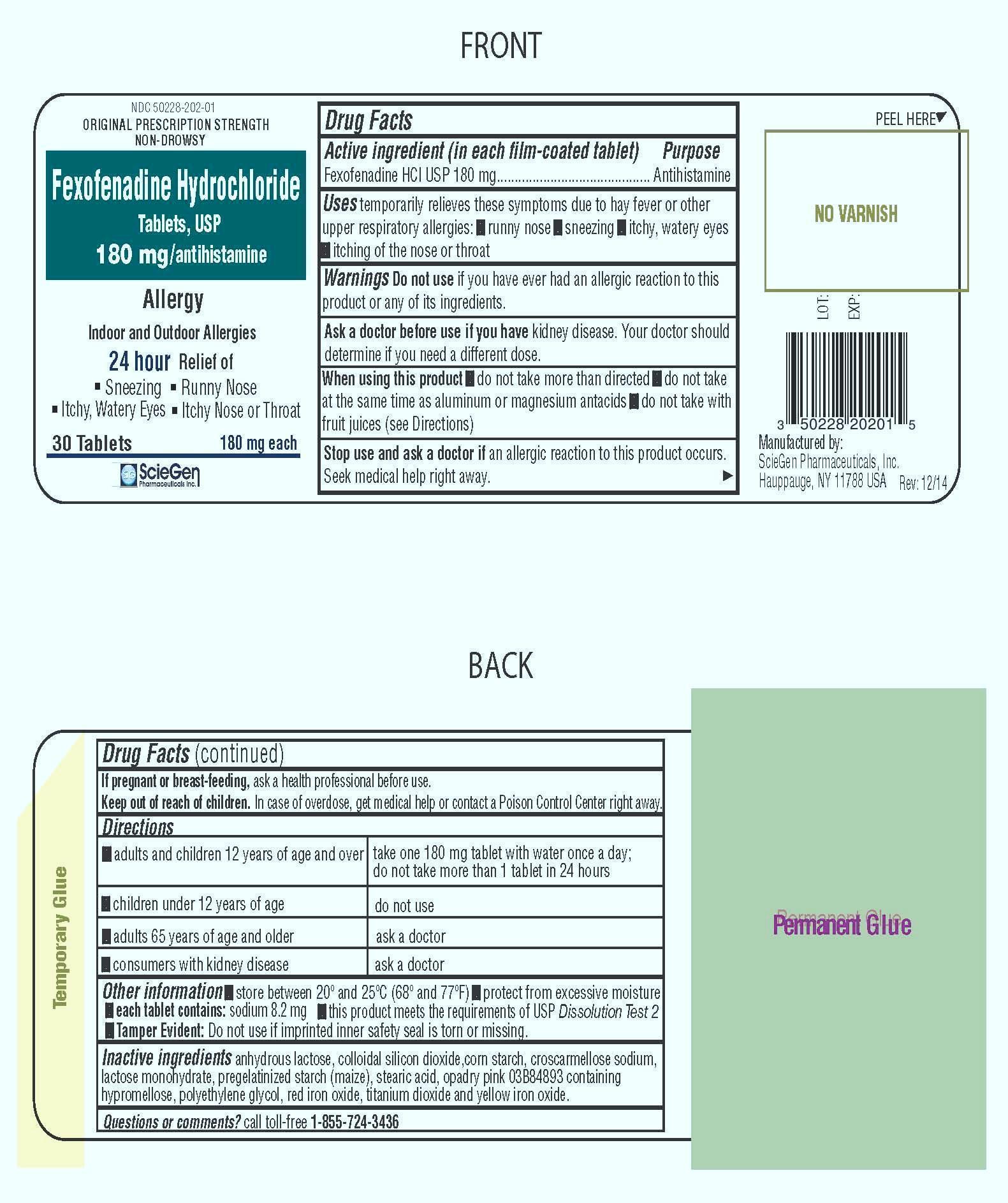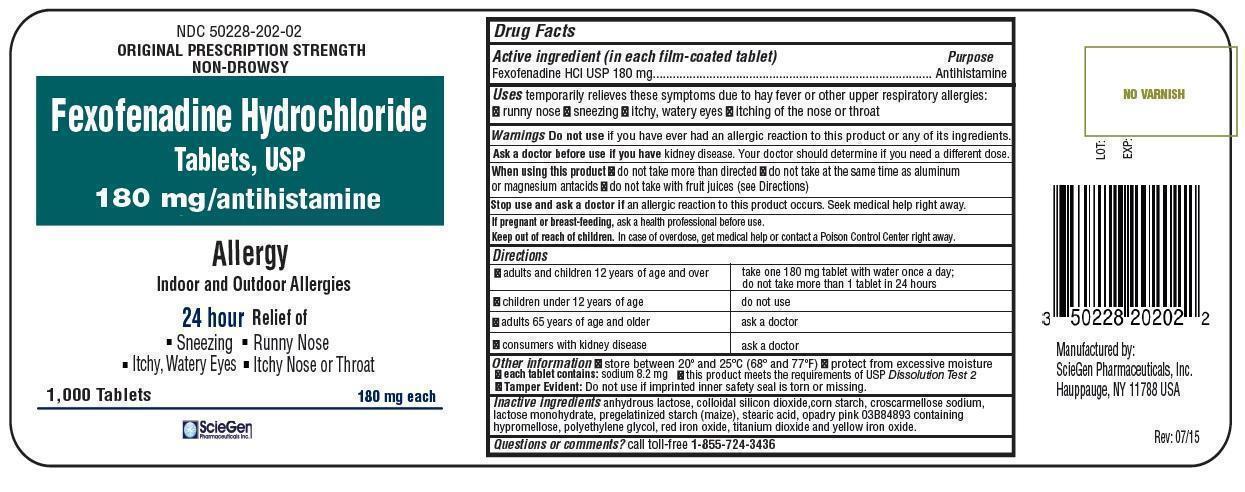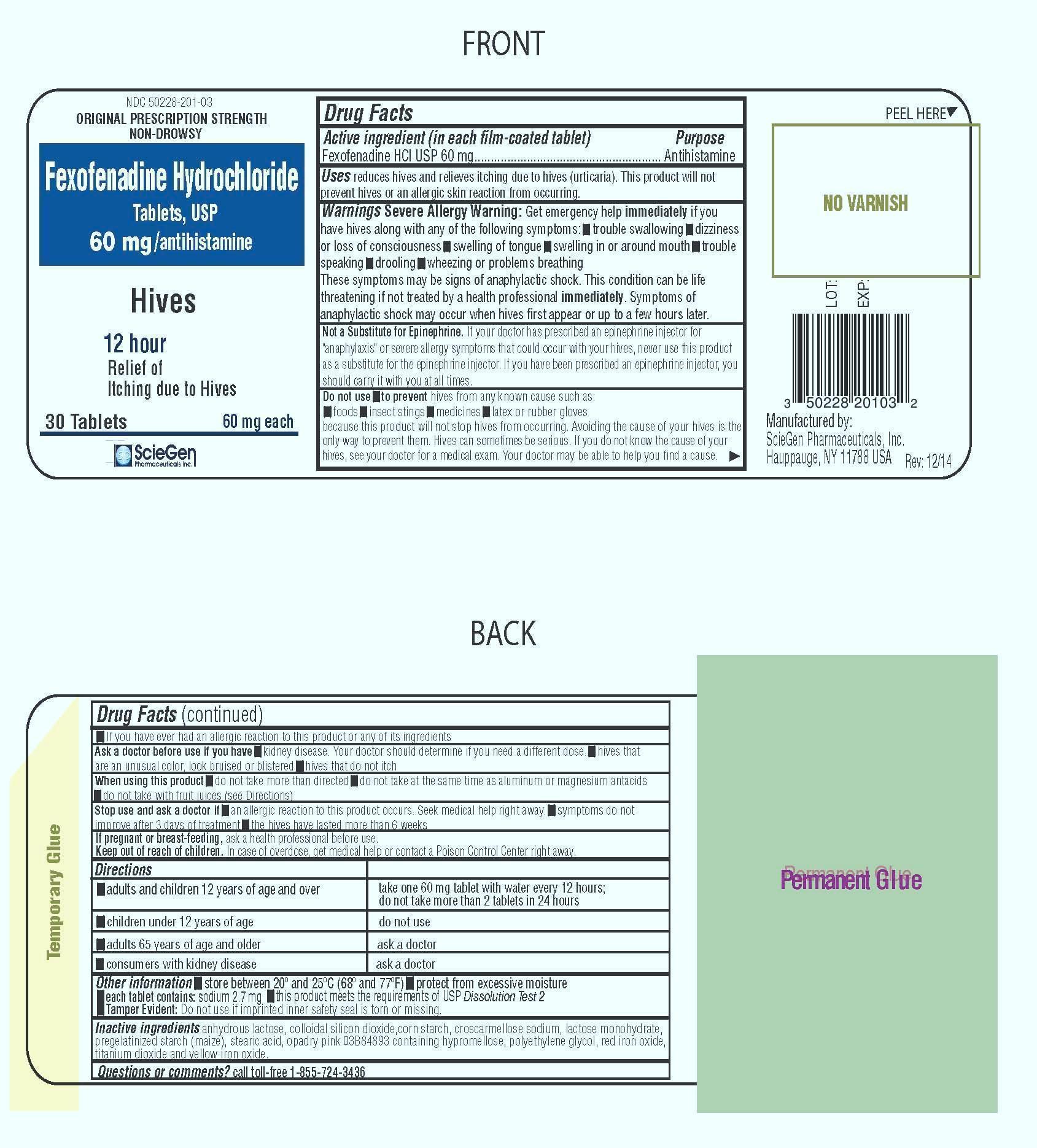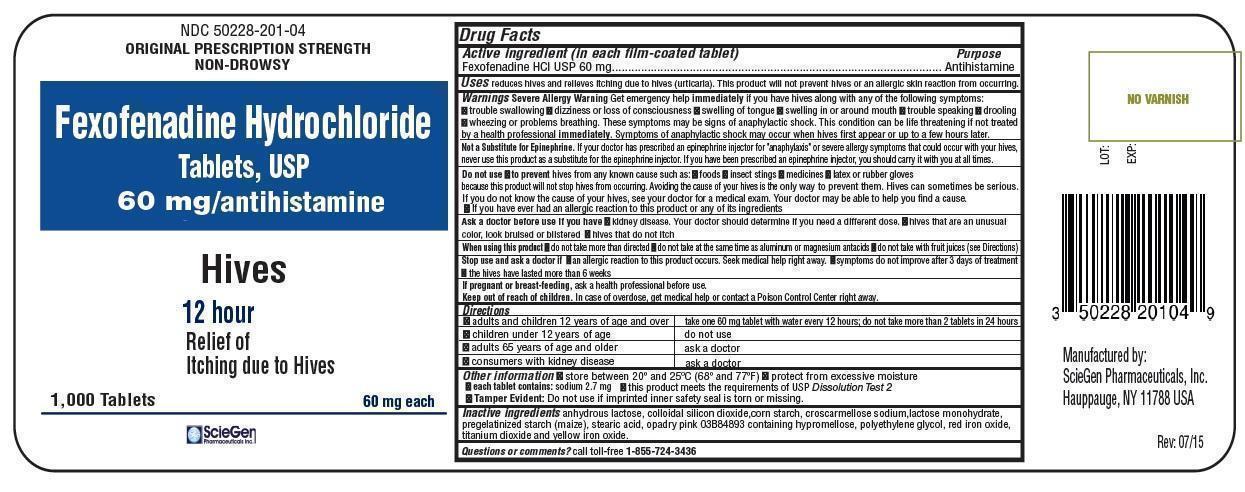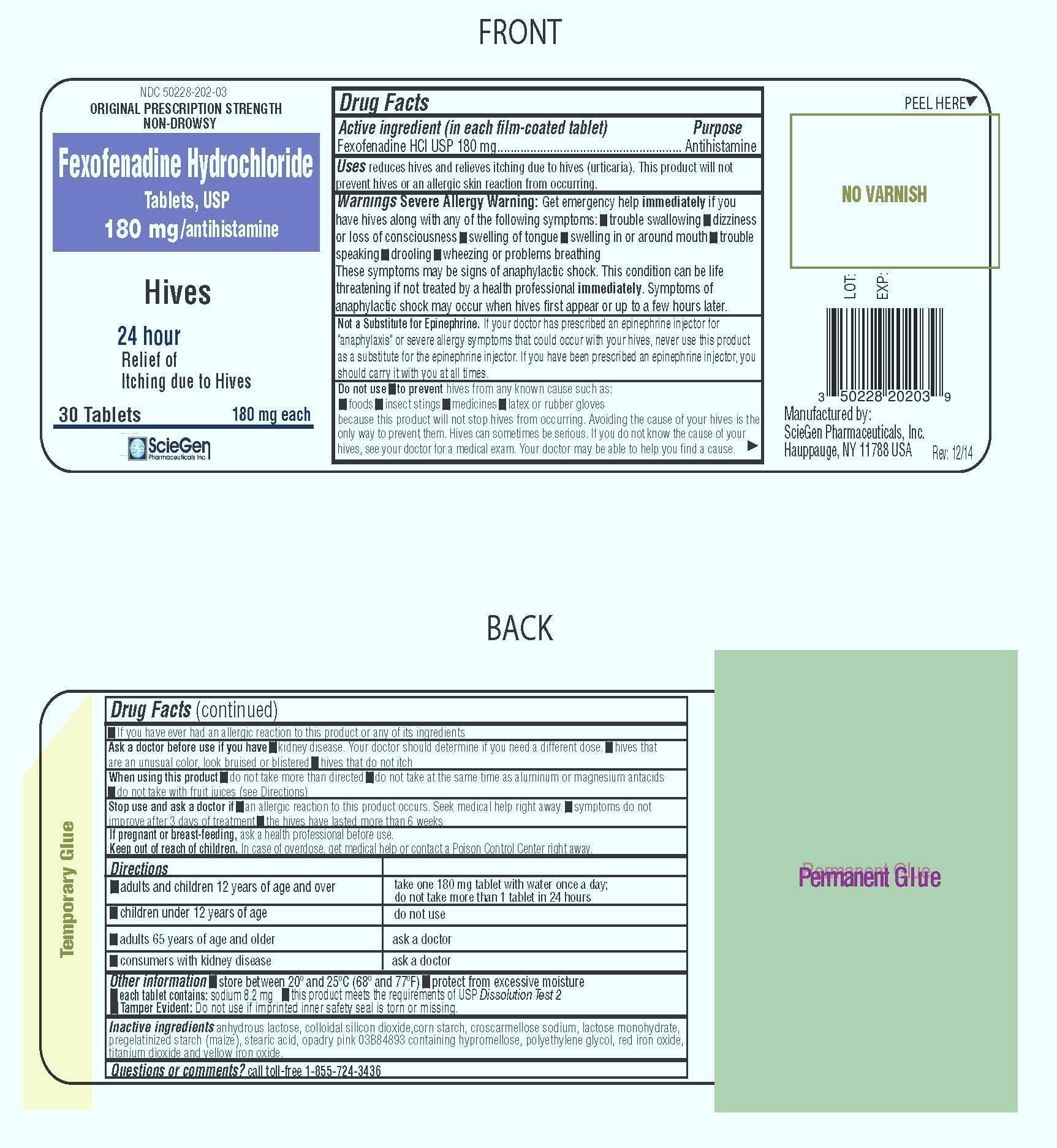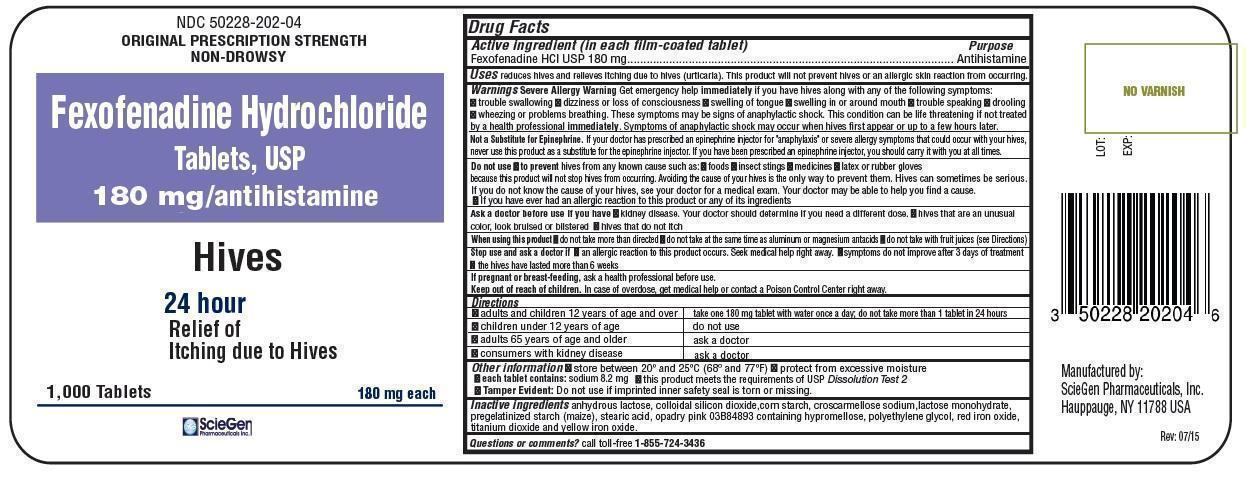 DRUG LABEL: fexofenadine hcl
NDC: 50228-201 | Form: TABLET, FILM COATED
Manufacturer: ScieGen Pharmaceuticals, Inc.
Category: otc | Type: HUMAN OTC DRUG LABEL
Date: 20241224

ACTIVE INGREDIENTS: FEXOFENADINE HYDROCHLORIDE 60 mg/1 1
INACTIVE INGREDIENTS: ANHYDROUS LACTOSE; SILICON DIOXIDE; STARCH, CORN; CROSCARMELLOSE SODIUM; LACTOSE MONOHYDRATE; STEARIC ACID; HYPROMELLOSE, UNSPECIFIED; POLYETHYLENE GLYCOL, UNSPECIFIED; FERRIC OXIDE RED; TITANIUM DIOXIDE; FERRIC OXIDE YELLOW

HIVES Active ingredient (in each film-coated tablet)

Fexofenadine HCl USP 60 mg

Fexofenadine HCl USP 180 mg

Purpose

Antihistamine

Uses

reduces hives and relieves itching due to hives (urticaria). This product will not prevent hives or an allergic skin reaction from occurring.

Warnings

WHEN USING

Severe Allergy Warning:Get emergency help immediatelyif you have hives along with any of the following symptoms:

- trouble swallowing
- dizziness or loss of consciousness
- swelling of tongue
- swelling in or around mouth
- trouble speaking
- drooling
- wheezing or problems breathing

These symptoms may be signs of anaphylactic shock. This condition can be life threatening if not treated by a health profession immediately.Symptoms of anaphylactic shock may occur when hives first appear or up to a few hours later.

Not a Substitute for Epinephrine.If your doctor has prescribed an epinephrine injector for "anaphylaxis" or severe allergy symptoms that could occur with your hives, never use this product as a substitute for the epinephrine injector. If you have been prescribed an epinephrine injector, you should carry it with you at all times.

Do not use

to preventhives from any known cause such as:

- foods
- insect stings
- medicines
- latex or rubber gloves

because this product will not stop hives from occurring. Avoiding the cause of your hives is the only way to prevent them. Hives can sometimes be serious. If you do not know the cause of your hives, see your doctor for a medical exam. Your doctor may be able to help you find a cause.

•If you have ever had an allergic reaction to this product or any of its ingredients

Ask a doctor before use if you have

- kidney disease.Your doctor should determine if you need a different dose.
- hives that are an unusual color, look bruised or blistered
- hives that do not itch

When using this product

- do not take more than directed
- do not take at the same time as aluminum or magnesium antacids
- do not take with fruit juices (see Directions)

Stop use and ask a doctor if

- an allergic reaction to this product occurs. Seek medical help right away.
- symptoms do not improve after 3 days of treatment
- the hives have lasted more than 6 weeks

If pregnant or breast-feeding,

ask a health professional before use.

Keep out of reach of children.

In case of overdose, get medical help or contact a Poison Control Center right away.

Directions (for 60mg)

adults and children 12 years of age and over | take one 60mg tablet with water every 12 hours; do not take more than 2 tablets in 24 hours
children under 12 years of age | do not use
adults 65 years of age and older | ask a doctor
consumers with kidney disease | ask a doctor

Directions (for 180mg)

adults and children 12 years of age and over | take one 180mg tablet with water once a day; do not take more than 1 tablet in 24 hours
children under 12 years of age | do not use
adults 65 years of age and older | ask a doctor
consumers with kidney disease | ask a doctor

Other information

- store between 20° and 25°C (68° and 77°F)
- protect from excessive moisture
- each tablet contains:sodium 2.7mg(for 60 mg), sodium 8.2mg(for 180 mg)
- this product meets the requirements of USP Dissolution Test 2
- Tamper Evident:Do not use if imprinted inner safety seal is torn or missing

Inactive ingredients

anhydrous lactose, colloidal silicon dioxide, corn starch, croscarmellose sodium, lactose monohydrate, pregelatinized starch(maize), stearic acid, opadry pink 03B84893 containing hypromellose, polyethylene glycol, red iron oxide titanium dioxide and yellow iron oxide.

Questions or comments?

Call toll-free 1-855-724-3436

Manufactured by:

ScieGen Pharmaceuticals, Inc.

Hauppauge, NY 11788 USA

ALLERGY Active ingredient (in each film-coated tablet)

Fexofenadine HCl USP 60 mg

Fexofenadine HCl USP 180 mg

Purpose

Antihistamine

Uses

temporarily relieves these symptoms due to hay fever or other upper respiratory allergies:

- runny nose
- sneezing
- itchy, watery eyes
- itching of the nose or throat

Warnings

Do not use

if you have ever had an allergic reaction to this product or any of its ingredients.

Ask a doctor before use if you have

kidney disease. Your doctor should determine if you need a different dose.

When using this product

- do not take more than directed
- do not take at the same time as aluminum or magnesium antacids
- do not take with fruit juices (see Directions)

Stop use and ask a doctor if

an allergic reaction to this product occurs. Seek medical help right away.

If pregnant or breast-feeding,

ask a health professional before use.

Keep out of reach of children.

In case of overdose, get medical help or contact a Poison Control Center right away.

Directions (for 60mg)

adults and children 12 years of age and over | take one 60mg tablet with water every 12 hours; do not take more than 2 tablets in 24 hours
children under 12 years of age | do not use
adults 65 years of age and older | ask a doctor
consumers with kidney disease | ask a doctor

Directions (for 180mg)

adults and children 12 years of age and over | take one 180mg tablet with water once a day; do not take more than 1 tablet in 24 hours
children under 12 years of age | do not use
adults 65 years of age and older | ask a doctor
consumers with kidney disease | ask a doctor

Other information

- store between 20° and 25°C (68° and 77°F)
- protect from excessive moisture
- each tablet contains:sodium 2.7mg(for 60 mg), sodium 8.2mg(for 180 mg)
- this product meets the requirements of USP Dissolution Test 2
- Tamper Evident:Do not use if imprinted inner safety seal is torn or missing

Inactive ingredients

anhydrous lactose, colloidal silicon dioxide, corn starch, croscarmellose sodium, lactose monohydrate, pregelatinized starch(maize), stearic acid, opadry pink 03B84893 containing hypromellose, polyethylene glycol, red iron oxide titanium dioxide and yellow iron oxide.

Questions or comments?

Call toll-free 1-855-724-3436

PACKAGE LABEL

Manufactured by:

ScieGen Pharmaceuticals, Inc.

Hauppauge, NY 11788 USA

Package/Label Principal Display Panel

Fexofenadine Hydrochloride Tablets USP 60mg

Package/Label Principal Display Panel

Fexofenadine Hydrochloride Tablets USP 180mg